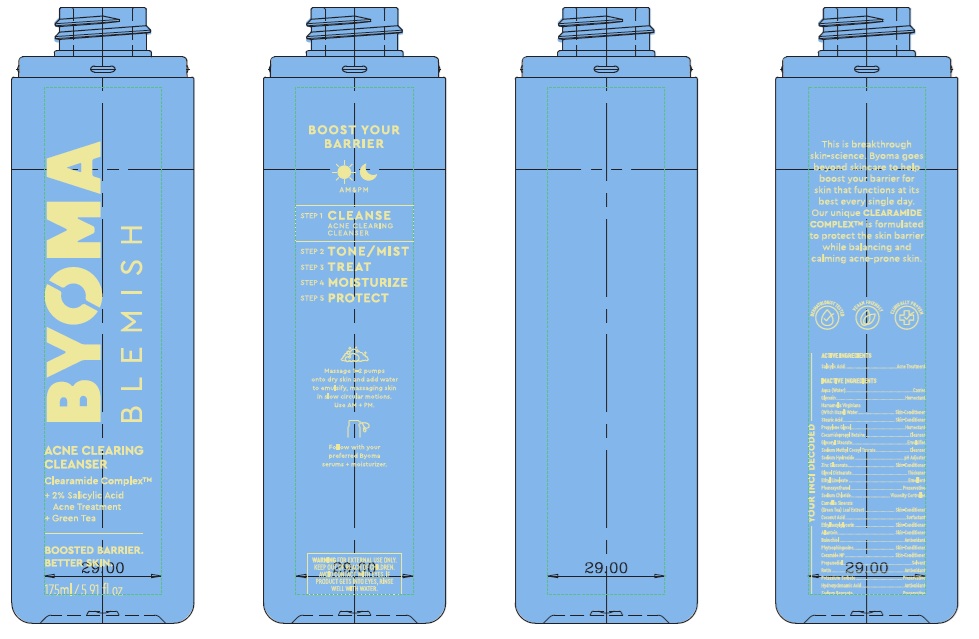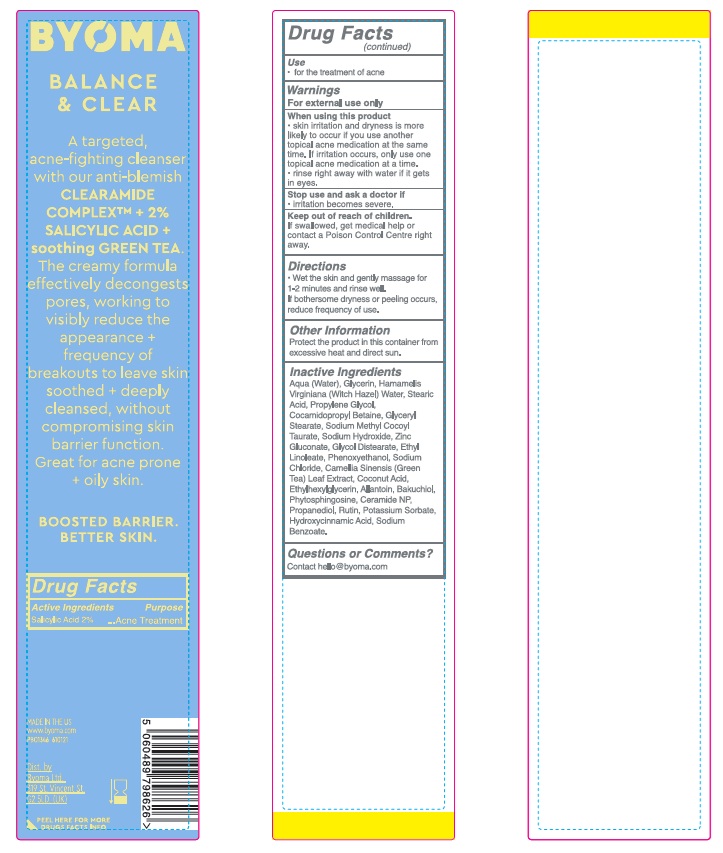 DRUG LABEL: Byoma Acne Clearing Cleanser
NDC: 84821-007 | Form: LIQUID
Manufacturer: Byoma Ltd
Category: otc | Type: HUMAN OTC DRUG LABEL
Date: 20250423

ACTIVE INGREDIENTS: SALICYLIC ACID 20 mg/1 mL
INACTIVE INGREDIENTS: SODIUM BENZOATE; PROPYLENE GLYCOL; WATER; BAKUCHIOL; HAMAMELIS VIRGINIANA TOP WATER; PHYTOSPHINGOSINE; COCAMIDOPROPYL BETAINE; SODIUM HYDROXIDE; COCONUT ACID; ETHYL LINOLEATE; GREEN TEA LEAF; POTASSIUM SORBATE; STEARIC ACID; GLYCERIN; SODIUM METHYL COCOYL TAURATE; ZINC GLUCONATE; PHENOXYETHANOL; GLYCOL DISTEARATE; HYDROXYCINNAMIC ACID; SODIUM CHLORIDE; ETHYLHEXYLGLYCERIN; ALLANTOIN; PROPANEDIOL; CERAMIDE NP; GLUCOMANNAN; RUTIN

Byoma Acne Clearing Cleanser

Active ingredient

Salicylic Acid 2%

Purpose

Acne Treatment

Use

- for the treatment of acne

Warnings

For external use only

When using this product

- skin irritation and dryness is more likely to occur if you use another topical acne medication at the same time. If irritation occurs, only use one topical acne medication at a time.
- rinse right away with water if it gets in eyes.

Stop use and ask a doctor if

- irritation becomes severe.

Keep out of reach of children.

If swallowed, get medical help or contact a Poison Control Centre right away.

Directions

- Wet the skin and gently massage for 1-2 minutes and rinse well.
- If bothersome dryness or peeling occurs, reduce frequency of use.

Other Information

Protect the product in this container from excessive heat and direct sun.

Inactive Ingredients

Aqua (Water), Glycerin, Hamamelis Virginiana (Witch Hazel) Water, Stearic Acid, Propylene Glycol, Cocamidopropyl Betaine, Glyceryl Stearate, Sodium Methyl Cocoyl Taurate, Sodium Hydroxide, Zinc Gluconate, Glycol Distearate, Ethyl Linoleate, Phenoxyethanol, Sodium Chloride, Camellia Sinensis (Green Tea) Leaf Extract, Coconut Acid, Ethylhexylglycerin, Allantoin, Bakuchiol, Phytosphingosine, Ceramide NP, Propanediol, Rutin, Potassium Sorbate, Hydroxycinnamic Acid, Sodium Benzoate.

Questions or Comments?

Contact hello@byoma.com